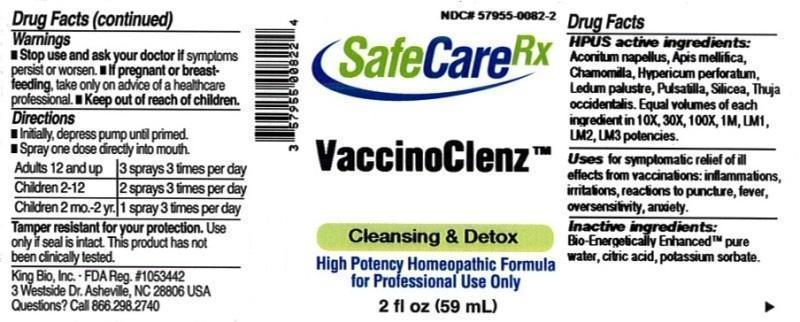 DRUG LABEL: VaccinoClenz
NDC: 57955-0082 | Form: LIQUID
Manufacturer: King Bio Inc.
Category: homeopathic | Type: HUMAN OTC DRUG LABEL
Date: 20150601

ACTIVE INGREDIENTS: ACONITUM NAPELLUS 10 [hp_X]/59 mL; APIS MELLIFERA 10 [hp_X]/59 mL; MATRICARIA RECUTITA 10 [hp_X]/59 mL; HYPERICUM PERFORATUM 10 [hp_X]/59 mL; LEDUM PALUSTRE TWIG 10 [hp_X]/59 mL; PULSATILLA VULGARIS 10 [hp_X]/59 mL; SILICON DIOXIDE 10 [hp_X]/59 mL; THUJA OCCIDENTALIS LEAFY TWIG 10 [hp_X]/59 mL
INACTIVE INGREDIENTS: WATER; ANHYDROUS CITRIC ACID; POTASSIUM SORBATE

VaccinoClenz™

ACTIVE INGREDIENT

Drug Facts__________________________________________________________________________________________________________

HPUS active ingredients: Aconitum napellus, Apis mellifica, Chamomilla, Hypericum perforatum, Ledum palustre, Pulsatilla, Silicea, Thuja occidentalis. Equal volumes of each ingredient in 10X, 30X, 100X, 1M, LM1, LM2, LM3 potencies.

INDICATIONS AND USAGE

Uses for symptomatic relief of ill effects from vaccinations: inflammations, irritations, reactions to puncture, fever, oversensitivity, anxiety.

Inactive Ingredients:

Bio-Energetically Enhanced™ pure water, citric acid and potassium sorbate.

Warnings

- Stop use and ask your doctor if symptoms persist or worsen.
- If pregnant or breast-feeding, take only on advice of a healthcare professional.

- Keep out of reach of children.

Directions

- Initially, depress pump until primed.
- Spray one dose directly into mouth.
- Adults 12 and up: 3 sprays 3 times per day.
- Children 2-12: 2 sprays 3 times per day.
- Children 2 mo.-2 yr: 1 spray 3 times per day.

OTHER SAFETY INFORMATION

Tamper resistant for your protection. Use only if safety seal is intact. This product has not been clinically tested.

PURPOSE

Uses for symptomatic relief of ill effects from vaccinations:

- inflammations
- irritations
- reactions to puncture
- fever
- oversensitivity
- anxiety